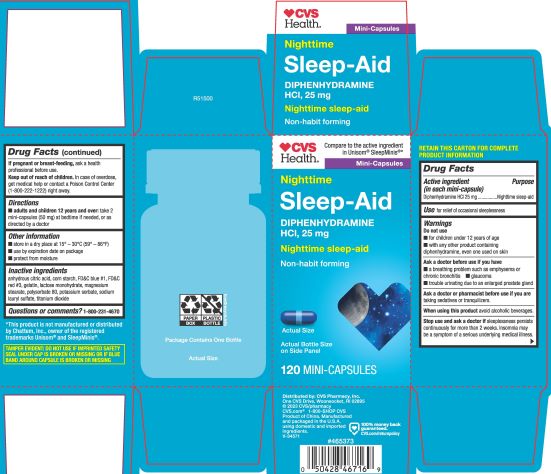 DRUG LABEL: Diphenhydramine Hydrochloride
NDC: 51316-347 | Form: CAPSULE
Manufacturer: CVS Pharmacy, Inc
Category: otc | Type: HUMAN OTC DRUG LABEL
Date: 20240212

ACTIVE INGREDIENTS: DIPHENHYDRAMINE HYDROCHLORIDE 25 mg/1 1
INACTIVE INGREDIENTS: FD&C BLUE NO. 1; LACTOSE MONOHYDRATE; GELATIN; MAGNESIUM STEARATE; TITANIUM DIOXIDE; POTASSIUM SORBATE; STARCH, CORN; SODIUM LAURYL SULFATE; FD&C RED NO. 3; ANHYDROUS CITRIC ACID; POLYSORBATE 80

5347K-CVS

Drug Facts

Active ingredient (in each mini-capsule)
Diphenhydramine HCl 25 mg

Purpose
Nighttime sleep-aid

Use

for relief of occasional sleeplessness

WARNINGS

DO NOT USE

- for children under 12 years of age
- with any other product containing diphenhydramine, even one used on skin

ASK DOCTOR

- a breathing problem such as emphysema or chronic bronchitis
- glaucoma
- trouble urinating due to an enlarged prostate gland

Ask a doctor or pharmacist before use if you are taking sedatives or tranquilizers.

When using this product avoid alcoholic beverages.

Stop use and ask a doctor if sleeplessness persists continuously for more than 2 weeks. Insomnia may be a symptom of a serious underlying medical illness.

PREGNANCY OR BREAST FEEDING

If pregnant or breast-feeding, ask a health professional before use.

Keep out of reach of children.

OVERDOSAGE

In case of overdose, get medical help or contact a Poison Control Center (1-800-222-1222) right away.

Directions

- adults and children 12 years and over: take 2 mini-capsules (50 mg) at bedtime if needed, or as directed by a doctor

Other information

- store in a dry place at 15° – 30°C (59° – 86°F)
- use by expiration date on package
- protect from moisture

INACTIVE INGREDIENT

anhydrous citric acid, corn starch, FD&C blue #1, FD&C red #3, gelatin, lactose monohydrate, magnesium stearate, polysorbate 80, potassium sorbate, sodium lauryl sulfate, titanium dioxide.

Questions or comments?

1-800-231-4670

Distributed by: CVS Pharmacy, Inc.
One CVS Drive, Woonsocket, RI 02895
© 2023 CVS/pharmacy
CVS.com® 1-800-SHOP CVS
Product of China. Manufactured and packaged in the U.S.A. using domestic and imported ingredients.
V-34571

*This product is not manufactured or distributed by Chattem, Inc., owner of the registered trademarks Unisom® and SleepMinis®.

TAMPER EVIDENT: DO NOT USE IF IMPRINTED SAFETY SEAL UNDER CAP IS BROKEN OR MISSING OR IF BLUE BAND AROUND CAPSULE IS BROKEN OR MISSING.

PACKAGE LABEL

Compare to the active ingredient in Unisom® SleepMinis®*

Nighttime
DIPHENHYDRAMINE HCl, 25 mg
Nighttime sleep-aid
Non-habit forming

120 MINI-CAPSULES